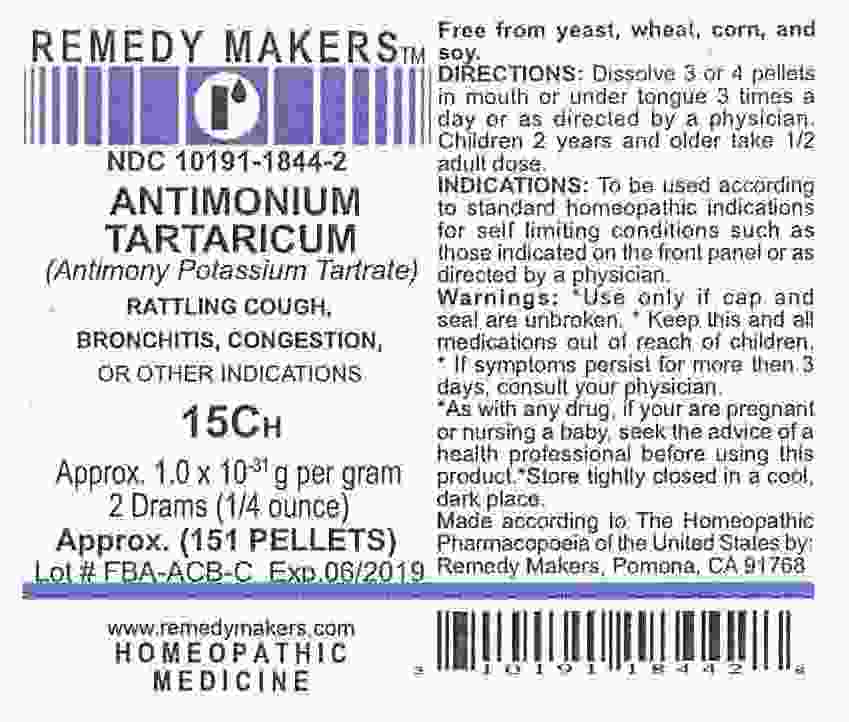 DRUG LABEL: ANTIMONIUM TARTARICUM
NDC: 10191-1844 | Form: PELLET
Manufacturer: Remedy Makers
Category: homeopathic | Type: HUMAN OTC DRUG LABEL
Date: 20100624

ACTIVE INGREDIENTS: ANTIMONY POTASSIUM TARTRATE 15 [hp_C]/1 1

ANTIMONIUM TARTARICUM 15C (Antimony Potassium Tartrate)

INDICATIONS AND USAGE

Free from yeast, wheat, corn, and soy.
DIRECTIONS: Dissolve 3 or 4 pellets
in mouth or under tongue 3 times a day or as directed by a physician.
Children 2 years and older take 1/2
adult dose.
INDICATIONS: To be used according
to standard homeopathic indications
for self limiting conditions such as
those indicated on the front panel or as directed by a physician.
Warnings: *Use only if cap and
seal are unbroken. * Keep this and all medications out of reach of children.
* If symptoms persist for more then 3
days, consult your physician.
*As with any drug, if your are pregnant or nursing a baby, seek the advice of a
health professional before using this product.*Store tightly closed in a cool, dark place.
Made according to The Homeopathic Pharmacopoeia of the United States by: Remedy Makers, Pomona, CA 91768